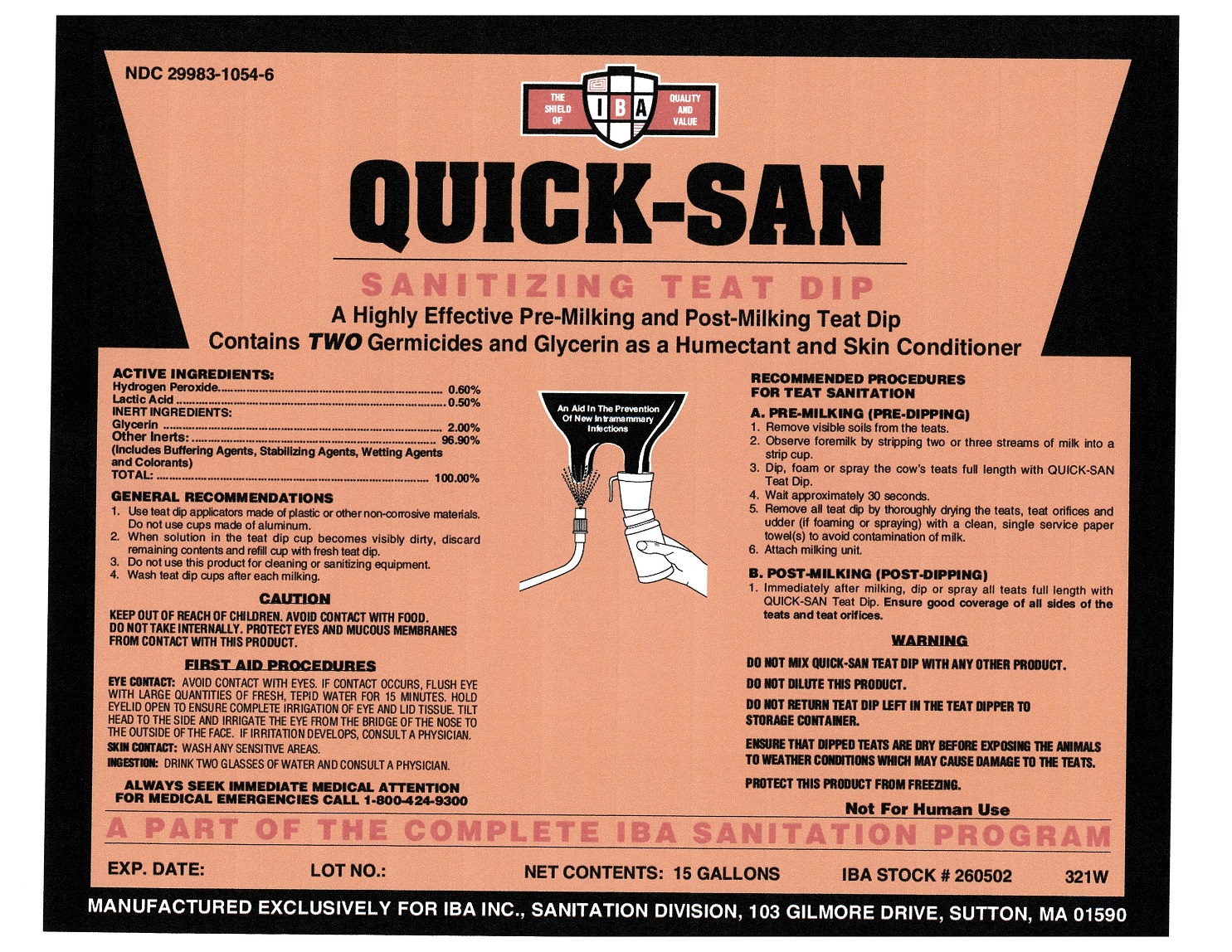 DRUG LABEL: QUICK-SAN
NDC: 29983-1054 | Form: LIQUID
Manufacturer: IBA
Category: animal | Type: OTC ANIMAL DRUG LABEL
Date: 20251211

ACTIVE INGREDIENTS: HYDROGEN PEROXIDE .60 kg/100 kg; LACTIC ACID .50 kg/100 kg

Quick-San

Active Ingredients

Hydrogen Peroxide..........................................................0.60%

Lactic Acid......................................................................0.50%

INERT INGREDIENTS:

Glycerin................................................................... .....2.00%

Other InertsL................................................................96.90%

(Includes Buffering Agents, Stabilizing Agents, Wetting Agents

and Colorants)

TOTAL...................................................................... ..100.00%

GENERAL RECOMMENDATION

1. Use teat dip applicators made of plastic or other non-corrosive materials. Do not use cups made of aluminum.

2. When solution in the teat dip cup becomes visibly dirty, discard remaining contents and refill cup with fresh teat dip.

3. Do not use this product for cleaning or sanitizing equipment.

4. Wash teat dip cups after each milking.

CAUTION

KEEP OUT OF REACH OF CHILDREN. AVOID CONTACT WITH FOOD.

DO NOT TAKE INTERNALLY. PROTECT EYES AND MUCOUS MEMBRANES

FROM CONTACT WITH THIS PRODUCT.

FIRST AID PROCEDURES

EYE CONTACT: AVOID CONTACT WITH EYES. IF CONTACT OCCURS, FLUSH EYE WITH LARGE QUANTITIES OF FRESH, TEPID WATER FOR 15 MINUTES. HOLD EYELID OPEN TO ENSURE COMPLETE IRRIGATION OF EYE AND LID TISSUE. TILT HEAD TO THE SIDE AND IRRIGATE THE EYE FROM THE BRIDGE OF THE NOSE TO THE OUTSIDE OF THE FACE. IF IRRIGATION DEVELOPS, CONSULT A PHYSICIAN.

SKIN CONTACT: WASH ANY SENSITIVE AREAS.

INGESTION: DRINK TWO GLASSES OF WATER AND CONSULT A PHYSICIAN.

ALWAYS SEEK IMMEDIATE MEDICAL ATTENTION

FOR MEDICAL EMERGENCIES CALL 1-800-424-9300

RECOMMENDED PROCEDURES FOR TEAT SANITATION

A. PRE-MILKING (PRE-DIPPING)

1. Remove visible soils from the teats.

2. Observe foremilk by stripping two or three streams of milk into a strip cup.

3. Dip, foam or spray the cow's teats full length with QUICK-SAN Teat Dip.

4. Wait approximately 30 seconds.

5. Remove all teat dip by thoroughly drying the teats, teat orifices and udder (if foaming or spraying) with a clean, single, service paper towerl(s) to avoid contamination of milk.

6. Attach milking unit.

B. POST-MILKING (POST-DIPPING)

1. Immediately after milking, dip or spray all teats full length with QUICK-SAN Teat Dip. Ensure good coverage of all sides of the teats and teat orifices.

WARNING

DO NOT MIX QUICK-SAN TEAT DIP WITH ANY OTHER PRODUCT.

DO NOT DILUTE THIS PRODUCT.

DO NOT RETURN TEAT DIP LEFT IN THE TEAT DIPPER TO STORAGE CONTAINER.

ENSURE THAT DIPPED TEATS ARE DRY BEFORE EXPOSING THE ANIMALS TO WEATHER CONDITIONS WHICH MAY CAUSE DAMAGE TO THE TEATS.

PROTECT THIS PRODUCT FROM FREEZING.

Not For Human Use